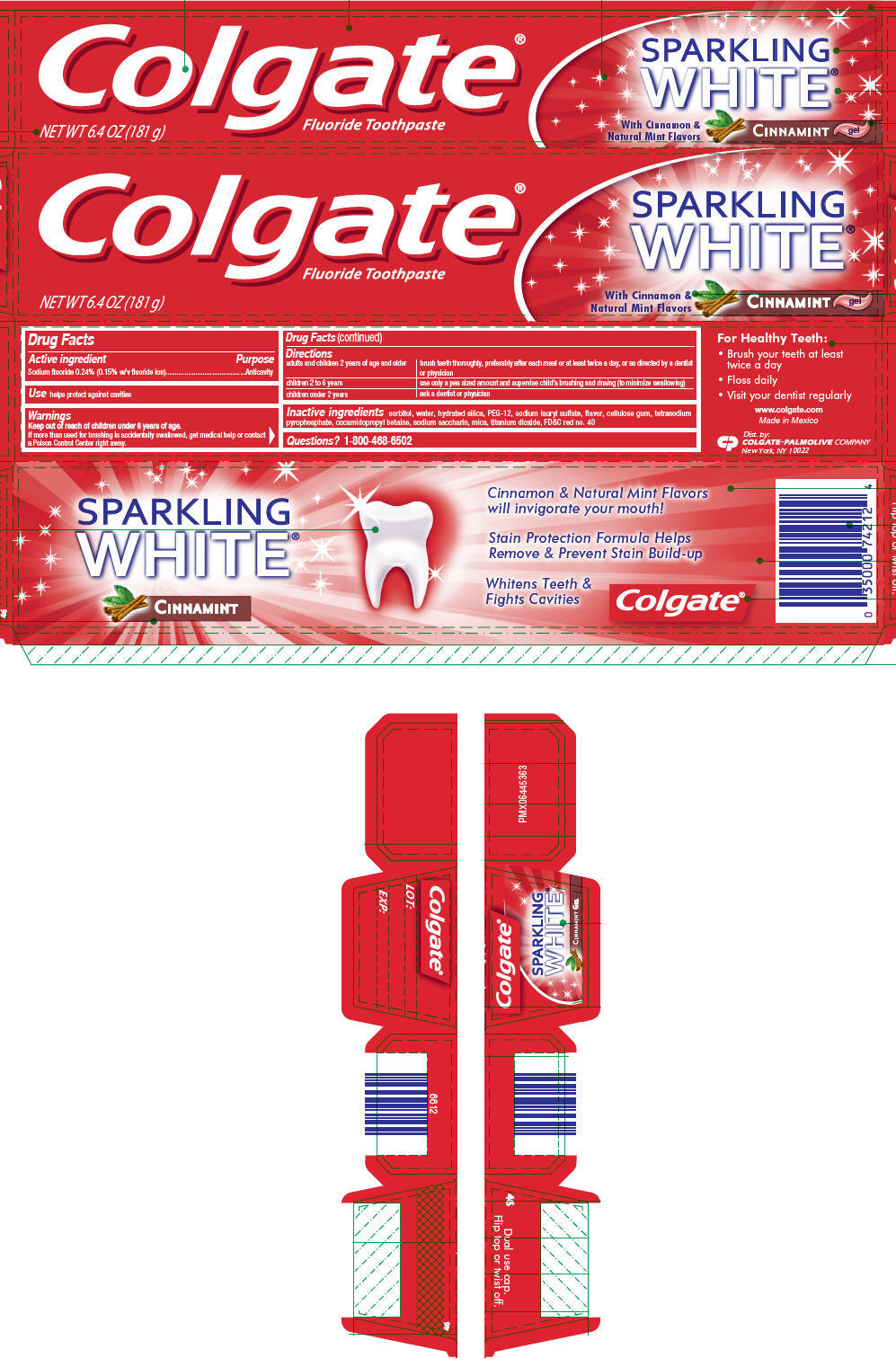 DRUG LABEL: COLGATE SPARKLING WHITE CINNAMINT
NDC: 35000-900 | Form: GEL, DENTIFRICE
Manufacturer: COLGATE PALMOLIVE COMPANY
Category: otc | Type: HUMAN OTC DRUG LABEL
Date: 20191127

ACTIVE INGREDIENTS: SODIUM FLUORIDE 1.1 mg/1 g
INACTIVE INGREDIENTS: SORBITOL 564.38 mg/1 g; WATER; HYDRATED SILICA; POLYETHYLENE GLYCOL 600; SODIUM LAURYL SULFATE; CARBOXYMETHYLCELLULOSE SODIUM, UNSPECIFIED; SODIUM PYROPHOSPHATE; COCAMIDOPROPYL BETAINE; SACCHARIN SODIUM; MICA; TITANIUM DIOXIDE; FD&C RED NO. 40

COLGATE® SPARKLING WHITE® CINNAMINT GEL

Drug Facts

Active ingredient

Sodium fluoride 0.24% (0.15% w/v fluoride ion)

Purpose

Anticavity

Use

helps protect against cavities

Warnings

Keep out of reach of children under 6 years of age.

If more than used for brushing is accidentally swallowed, get medical help or contact a Poison Control Center right away.

Directions

adults and children 2 years of age and older | brush teeth thoroughly, preferably after each meal or at least twice a day, or as directed by a dentist or physician
children 2 to 6 years | use only a pea sized amount and supervise child's brushing and rinsing (to minimize swallowing)
children under 2 years | ask a dentist or physician

Inactive ingredients

sorbitol, water, hydrated silica, PEG-12, sodium lauryl sulfate, flavor, cellulose gum, tetrasodium pyrophosphate, cocamidopropyl betaine, sodium saccharin, mica, titanium dioxide, FD&C red no. 40

Questions?

1-800-468-6502

Dist. by:
COLGATE-PALMOLIVE COMPANY
New York, NY 10022

PRINCIPAL DISPLAY PANEL - 181 g Tube Carton

Colgate®
Fluoride Toothpaste

SPARKLING
WHITE®

With Cinnamon &
Natural Mint Flavors

CINNAMINT
gel

NET WT 6.4 OZ (181 g)